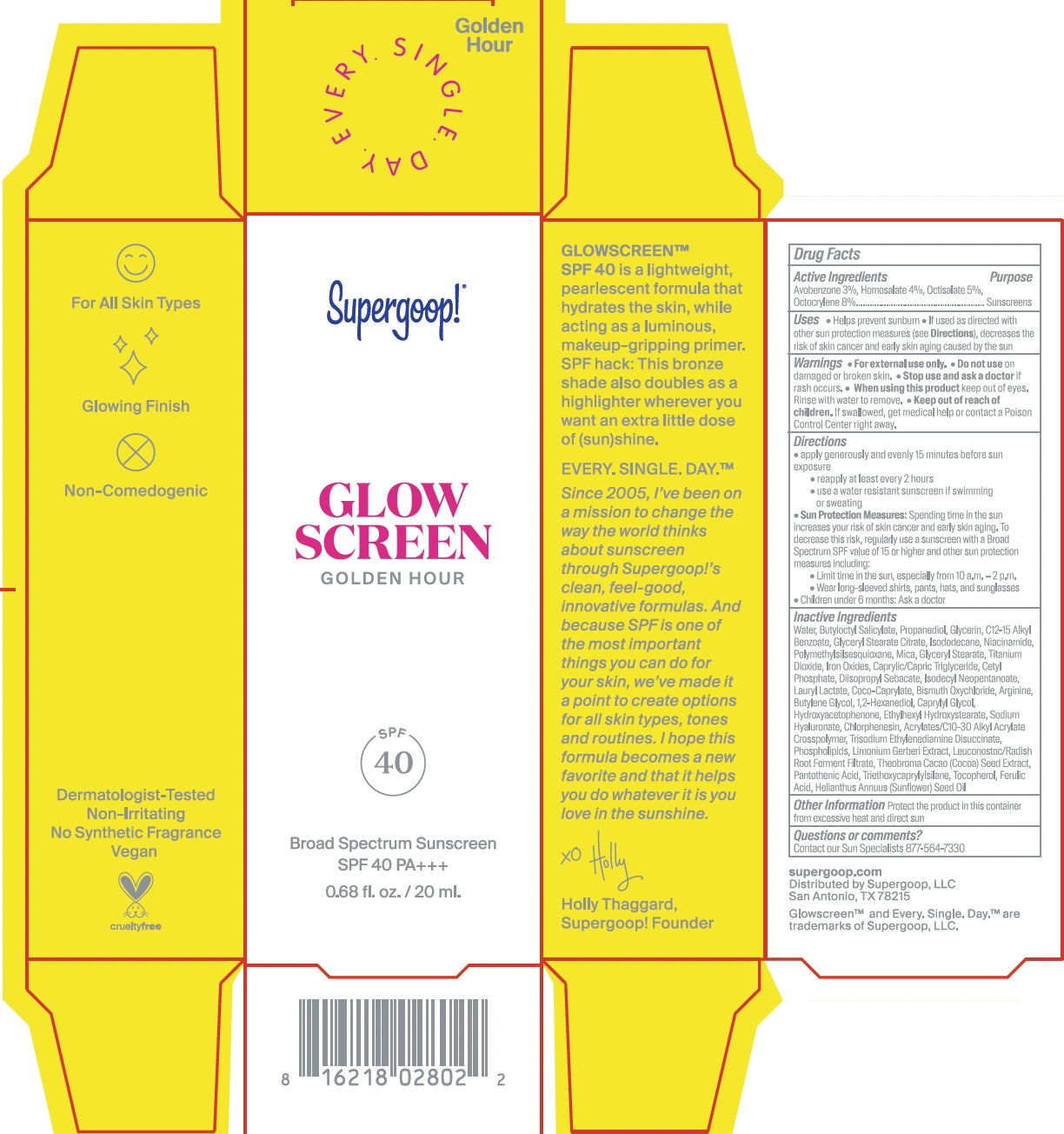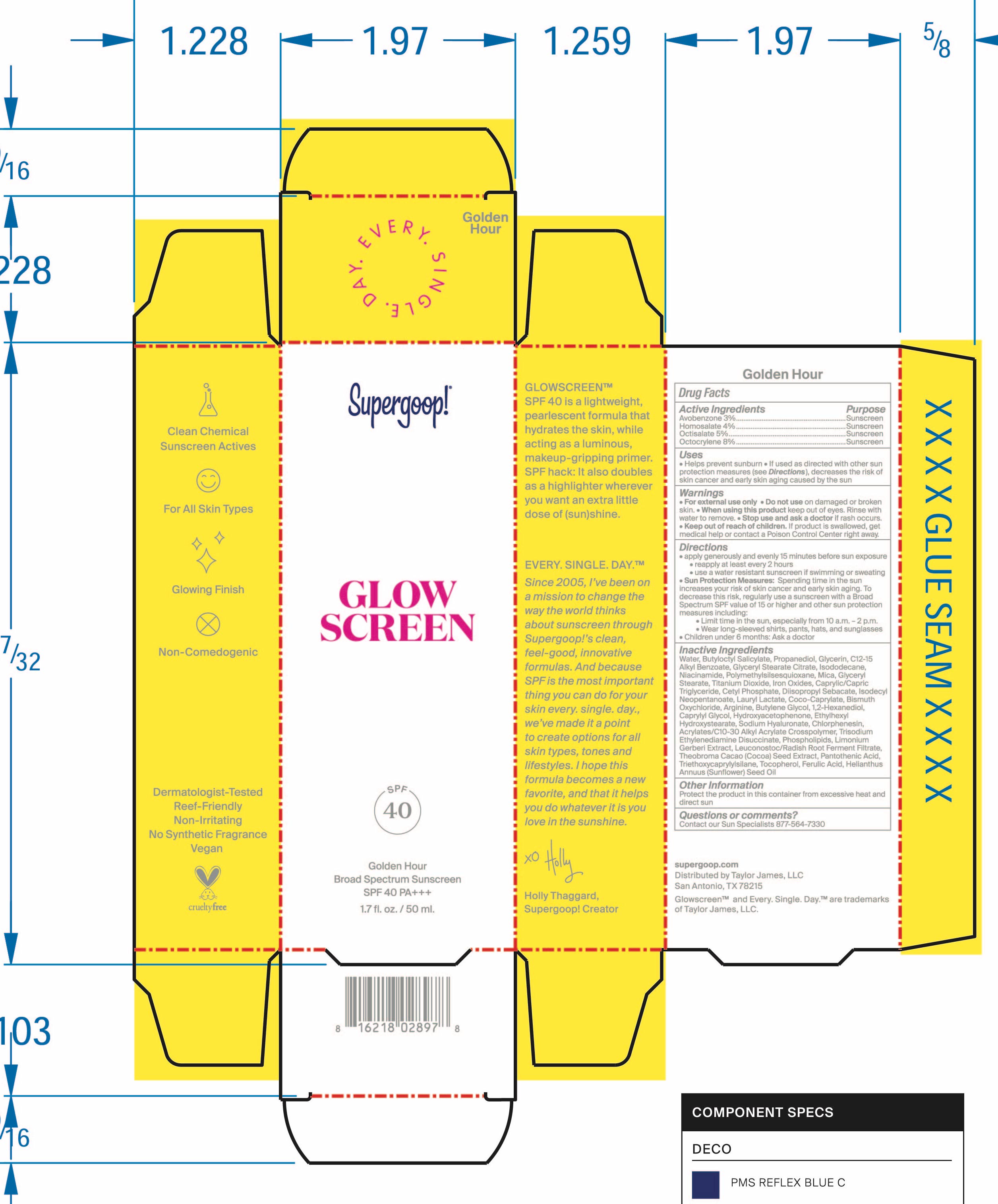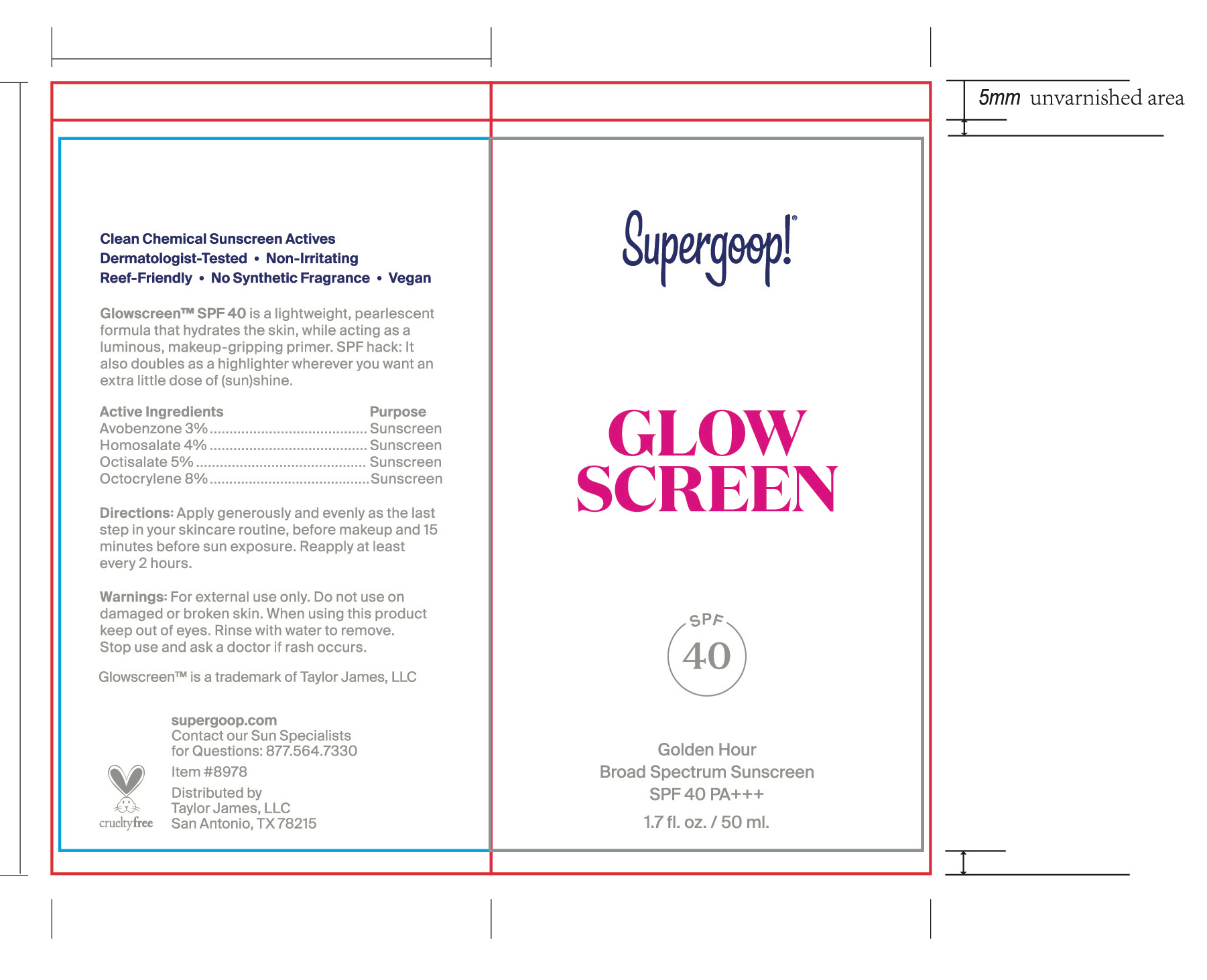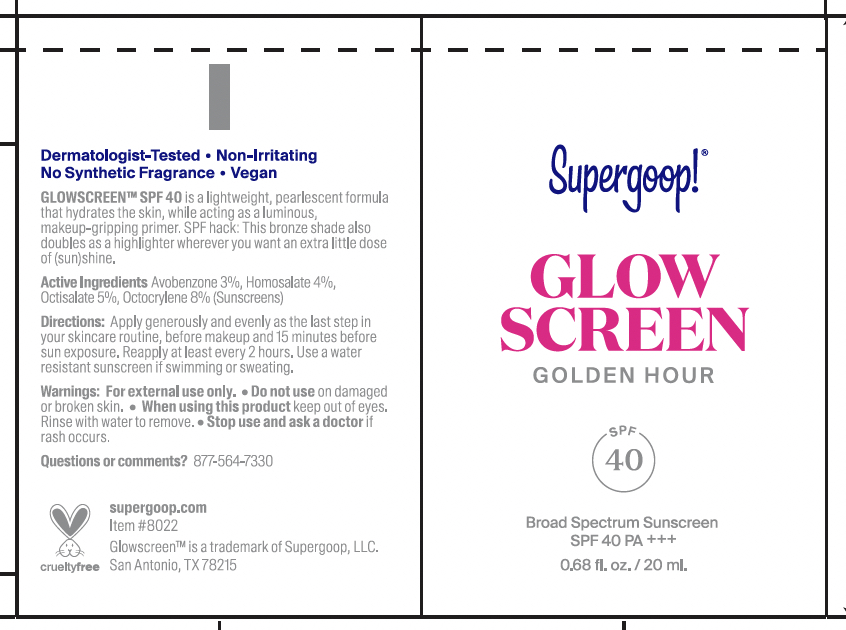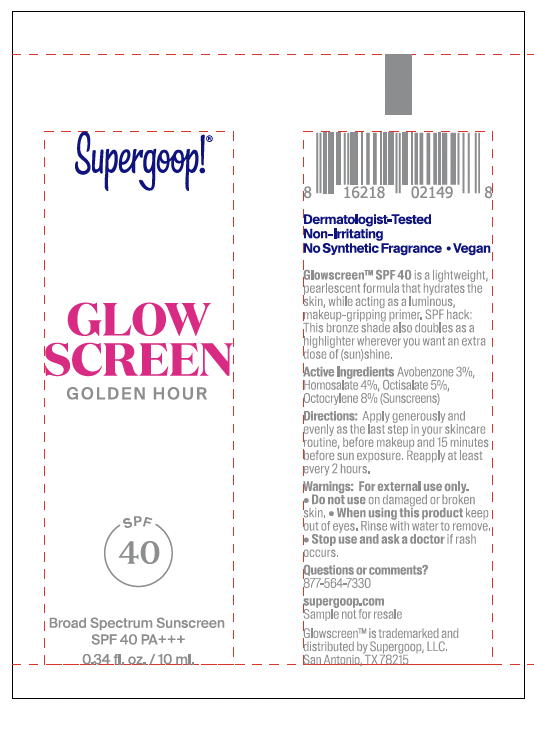 DRUG LABEL: Supergoop Glow Screen SPF 40
NDC: 75936-601 | Form: CREAM
Manufacturer: Supergoop LLC
Category: otc | Type: HUMAN OTC DRUG LABEL
Date: 20241205

ACTIVE INGREDIENTS: AVOBENZONE 3 mg/100 mL; OCTISALATE 5 mg/100 mL; HOMOSALATE 4 mg/100 mL; OCTOCRYLENE 8 mg/100 mL
INACTIVE INGREDIENTS: LEUCONOSTOC/RADISH ROOT FERMENT FILTRATE; PANTOTHENIC ACID; FERULIC ACID; ETHYLHEXYL HYDROXYSTEARATE; HYALURONATE SODIUM; TOCOPHEROL; SUNFLOWER OIL; GLYCERYL MONO- AND DICAPRYLOCAPRATE; COCO-CAPRYLATE; BISMUTH OXYCHLORIDE; CHLORPHENESIN; THEOBROMA CACAO WHOLE; TRIETHOXYCAPRYLYLSILANE; CETYL PHOSPHATE; DIISOPROPYL SEBACATE; ISODECYL NEOPENTANOATE; LAURYL LACTATE; ARGININE; BUTYLENE GLYCOL; 1,2-HEXANEDIOL; TRISODIUM ETHYLENEDIAMINE DISUCCINATE; GLYCERIN; MICA; TITANIUM DIOXIDE; POLYMETHYLSILSESQUIOXANE (11 MICRONS); GLYCERYL STEARATE SE; NIACINAMIDE; BROWN IRON OXIDE; BUTYLOCTYL SALICYLATE; PROPANEDIOL; GLYCERYL STEARATE CITRATE; ISODODECANE; CAPRYLYL GLYCOL; HYDROXYACETOPHENONE; WATER; C12-20 ALKYL BENZOATE; LIMONIUM GERBERI WHOLE

Supergoop Glow Screen SPF 40

Active Ingredients

Active Ingredients Purpose Avobenzone 3% Sunscreen Homosalate 4% Sunscreen Octisalate 5% Sunscreen Octocrylene 8% Sunscreen

Purpose

Uses Helps prevent sunburn If used as directed with other sun protection measures (see Directions), decreases

the risk of skin cancer and early skin aging caused by the sun

Keep out of reach of children. If product is swallowed, get medical help or contact a Poison Control Center right away

Indications and Usage

Stop use and ask a doctor if rash occurs

Warnings

For external use only
Do not use on damaged or broken skin
When using this product keep out of eyes. Rinse with water to remove

Dosage and Administration

Apply generously and evenly 15 minutes before sun exposure
rRapply at least every 2 hours
Use a water resistant Sunscreen if swimming or sweating
Sun Protection Measures Spending time in the sun increases your risk of skin
cancer and early skin aging. To decrease this risk, regularly use a sunscreen with a
Broad Spectrum SPF value of 15 or higher and other sun protection measures
including Limit time in the sun, especially from 10 a.m. - 2 p.m. Wear long-sleeved shirts, pants, hats, and sun glasses
Children under 6 months: Ask a doctor

Inactive Ingrediens

Water, Butyloctyl Salicylate , Propanediol, Glycerin, C12-C15 Alkyl Benzoate, Blyceryl Stearate Citrate, Isododecane, Niacinamide, Polymethylsilsesquioxane, Mica, Glyceryl Stearate, Titanium Dioxide, Iron Oxides, Caprylic/Capric Triglyceride, Cetyl Phosphate, Diisopropyl Sabacate, Isododecyl Neopentanoate, Lauryl Lactate, Coco-Caprylate, Bismuth Oxychloride, Arginine, Butylene Glycol, 1,2-Hexanediol, Caprylyl Glycol, Hydroxyacetophenone, Ethylhexyl Hudroxystearate, Sodium Hyaluronate, Chlorphenesin, Acrylates/C10-C30 Alkyl Acrylate Crosspolymer, Trisodium Ethylenediamine Disuccinate, Phospholipds, Limonium Gerberi Extract, Leuconostoc/Radish Root Ferment Filtrate, Theobroma Cacao (Cocoa) Seed Extract, Pantothenic Acid, Triethoxycprylylsilane, Tocopherol, Ferulic Acid, Helianthus Annus (Sunflower) Seed Oil

Package Label/PDP

Supergoop! Glow Screen SPF 40 GoldenHour Broad Spectrum Sunscren SPF 40 PA +++ 1.7 fl. oz. / 50 mL

Supergoop! Glowscreen Golden Hour 20 ml

Supergoop! Glowscreen Golden Hour 10 ml